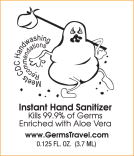 DRUG LABEL: Instant Hand Sanitizer
NDC: 50167-7100 | Form: GEL
Manufacturer: Germs Travel, LLC
Category: otc | Type: HUMAN OTC DRUG LABEL
Date: 20091202

ACTIVE INGREDIENTS: Alcohol .60 g/1 1
INACTIVE INGREDIENTS: Aloe; D&C Green no. 5; D&C Yellow no. 10; water

Instant Hand Sanitizer

Active ingredient

Ethyl Alcohol 66.5%

Purpose

Antiseptic

Uses

- for handwashing to decrease bacteria on skin without soap and water
- recommended for repeated use

Warnings

For external use only

Flammable, keep away from fire or flame

Do not use in the eyes. If this happens, rinse thoroughly with water

Stop use and ask a doctor If irritation and redness develop and persists for more than 72 hours

Keep out of reach of children If ingested get medical help or contact a Poison Control Center right away

Directions

- wet hands thoroughly with product
- allow to dry without wiping
- children under 6 should be supervised while using this product

INACTIVE INGREDIENT

Inactive ingredients aloe vera, carbomer, D&C green #5, D&C yellow #10, fragrance, purified water, triethanolamine

Manufactured for GERMS TRAVEL, LLC

Voorhees, NJ 08043 • 877-422-2928 • www.GermsTravel.com

PACKAGE LABEL - PRINCIPAL DISPLAY PANEL – POUCH

Instant Hand Sanitizer

Kills 99.99% of germs

Enriched with Aloe Vera

www.GermsTravel.com

0.125 FL. OZ (3.7 ML)